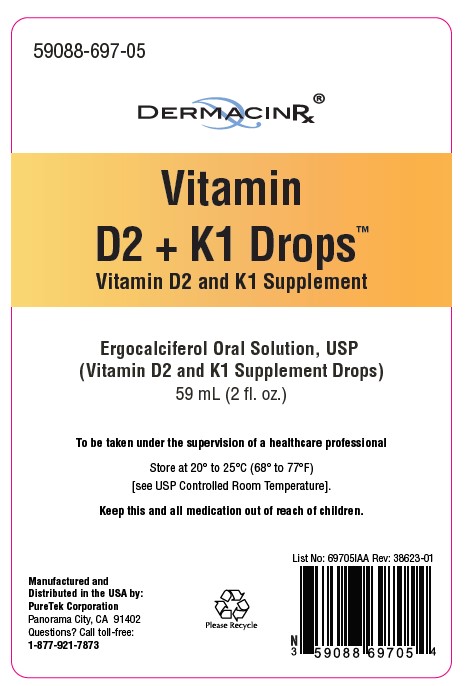 DRUG LABEL: Vitamin D2 and K1
NDC: 59088-697 | Form: LIQUID
Manufacturer: PURETEK CORPORATION
Category: other | Type: Dietary Supplement
Date: 20240307

ACTIVE INGREDIENTS: ERGOCALCIFEROL 20 ug/0.1 mL; PHYTONADIONE 120 ug/0.1 mL
INACTIVE INGREDIENTS: MEDIUM-CHAIN TRIGLYCERIDES

Vitamin D2 and K1 Drops

Vitamin D2 and K1 Supplement

Each mL of Vitamin D2 and K1 drops contains:

Vitamin D2 (as Ergocalciferol)…………………20 mcg (800 IU)

Vitamin K1 ……………………………………………………………120 mcg

Other Ingredients:

Caprylic Capric Triglyceride, Citrus Flavor.

Dosage:

Usual Adult dose is four drops once daily, or as prescribed by a licensed medical practitioner. If you
are pregnant or nursing, ask a healthcare professional.

Directions:

Take orally or mix with beverage.

Warning:

KEEP THIS AND ALL MEDICATIONS OUT OF THE REACH OF CHILDREN.
In case of accidental overdose, contact your healthcare provider or a poison control center
immediately.

PRECAUTIONS

Vitamin D2 + K1 Drops™ should be administered under the supervision of a licensed medical
practitioner.

Do not use if bottle seal is broken
Store at controlled room temperature 20º to 25ºC (68º to 77ºF). [See USP]. Protect from light and
moisture and avoid excessive heat.

How Supplied:

Vitamin D2 + K1 Drops™ is a light yellow liquid, available in a 60 mL (2 fl. oz.) bottle with a
dropper. NHRIC 59088-697-05.